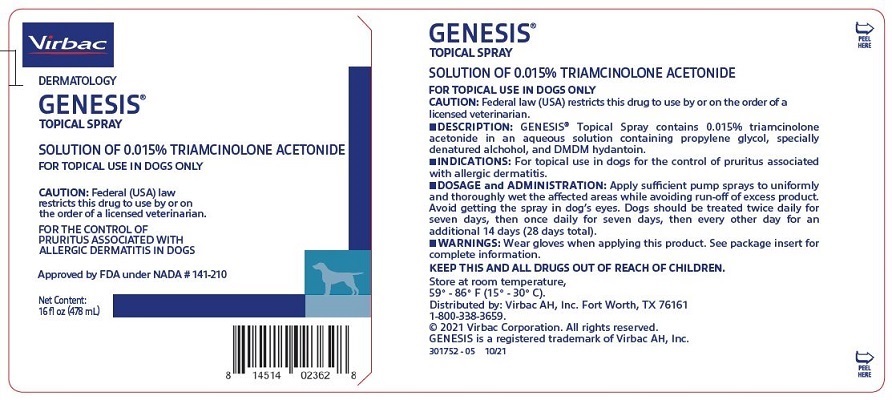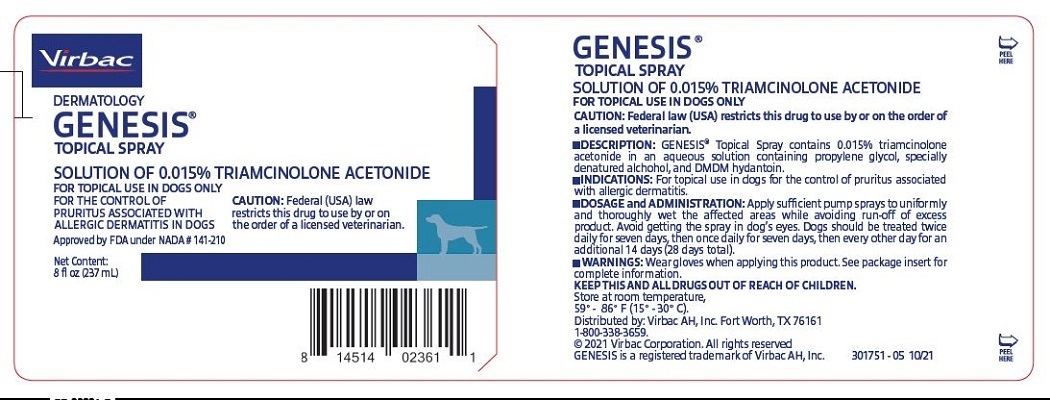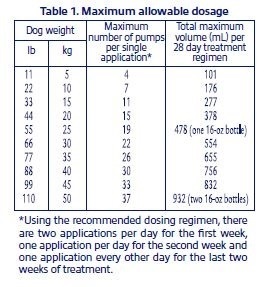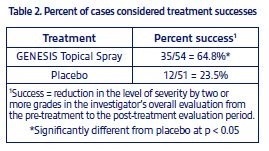 DRUG LABEL: Genesis
NDC: 51311-105 | Form: SPRAY
Manufacturer: Virbac AH, Inc.
Category: animal | Type: PRESCRIPTION ANIMAL DRUG LABEL
Date: 20220421

ACTIVE INGREDIENTS: TRIAMCINOLONE ACETONIDE 0.15 mg/1 mL

Genesis Topical Spray

Approved by FDA under NADA # 141-210

GENESIS®
TOPICAL SPRAY
Solution of 0.015% triamcinolone acetonide

FOR TOPICAL USE IN DOGS ONLY

PRECAUTIONS

CAUTION: Federal law (USA) restricts this drug to use by or on the order of a licensed veterinarian.

DESCRIPTION

GENESIS® Topical Spray contains 0.015% triamcinolone acetonide for dermatologic use. Each mL of GENESIS Topical Spray contains 0.15 mg triamcinolone acetonide in an aqueous solution containing propylene glycol, specially denatured alcohol, and DMDM hydantoin.

PHARMACOLOGY

Triamcinolone acetonide is a highly potent synthetic glucocorticoid, which is primarily effective because of its anti-inflammatory activity. Topical corticosteroids can be absorbed from normal intact skin. Studies have demonstrated that topical preparations of triamcinolone have decreased plasma cortisol levels and suppressed the response to ACTH.

INDICATIONS

GENESIS Topical Spray is indicated for the control of pruritus associated with allergic dermatitis in dogs.

DOSAGE AND ADMINISTRATION

Apply suffcient pump sprays to uniformly and thoroughly wet the affected areas while avoiding run-off of excess product. Avoid getting the spray in dog’s eyes. GENESIS Topical Sprays should be administered twice daily for seven days, once daily for the next seven days, then every other day for an additional 14 days (28 days total).

To avoid overdosing the product, use the following table to determine the maximum number of pump sprays per treatment application. For mild pruritus or for small treatment surface areas, the number of pumps used should be less than this maximum amount.

WARNINGS

User Safety: Wear gloves when applying the product. Spray in a well ventilated area. If the spray causes irritation to mucous membranes, discontinue use.

Keep this and all drugs out of reach of children.

Animal Safety: Clinical and experimental data have demonstrated that corticosteroids administered orally or by injection to animals may induce the first stage of parturition if used during the last trimester of pregnancy and may precipitate premature parturition followed by dystocia, fetal death, retained placenta, and metritis. Additionally, corticosteroids administered to dogs, rabbits, and rodents during pregnancy have resulted in cleft palates in offspring. Corticosteroids administered to dogs during pregnancy have also resulted in other congenital anomalies including deformed forelegs, phocomelia, and anasarca.

PRECAUTIONS

The safety of this product for dogs less than eight pounds or for dogs less than one year of age has not been evaluated. The safety of this product in breeding, pregnant or lactating dogs has not been evaluated (see WARNINGS). The safety of long term or repeated use of this product (greater than 28 days) has not been evaluated. Prolonged use or overdosage of any corticosteroid may produce adverse effects. Because absorption of triamcinolone acetonide through topical application on the skin and by licking may occur, dogs receiving triamcinolone acetonide therapy should be observed closely for evidence of hypothalamic-pituitary-adrenal (HPA) axis suppression. When the product was applied at approximately 6 times the maximum allowable dose (100 mL) once daily to normal skin of two dogs for five days, plasma cortisol levels were decreased after the first treatment and response to ACTH was reduced.

If adverse clinical signs are observed, treatment should be discontinued. Once the signs have disappeared, treatment can be resumed at a lower dose or frequency of application. If hypersensitivity to the product occurs, treatment should be discontinued and appropriate therapy instituted. In the presence of dermatological infections, use of an appropriate antifungal or antibacterial agent should be instituted. If a favorable response does not occur promptly, the corticosteroid should be discontinued until the infection has been adequately controlled.

ADVERSE REACTIONS

In a field study with GENESIS Topical Spray, polyuria was reported in 3 of 57 dogs (5.3%) and polyphagia in 1 of 57 dogs (1.8%). Mild (within reference range) decreases in total leukocyte, lymphocyte and eosinophil counts were also reported. The following local reactions were reported in ≤ 3.6% of 110 dogs treated with GENESIS Topical Spray or the product vehicle: aversion/discomfort, sneezing and watery eyes.

EFFECTIVENESS

In a 28-day field study to demonstrate the effectiveness of GENESIS Topical Spray in controlling pruritus associated with allergic dermatitis in dogs under field conditions, 105 dogs with atopy, unspecified allergic dermatitis, flea allergy, and food allergy were treated with GENESIS Topical Spray at the recommended use level or placebo. Results are shown in Table 2.

STORAGE CONDITIONS

Store at room temperature, 15° - 30° C (59° - 86° F).

HOW SUPPLIED

GENESIS Topical Spray is supplied in 8 ounce (237 mL) and 16 ounce (478 mL) bottles with spray applicators.

For technical information or to report adverse reactions, please call 1-800-338-3659.

Distributed by:
Virbac AH, Inc.
Fort Worth, TX 76161
© 2021 Virbac Corporation. All rights reserved.
GENESIS is a registered trademark of Virbac AH, Inc.

Rev. 10/21 750033-05